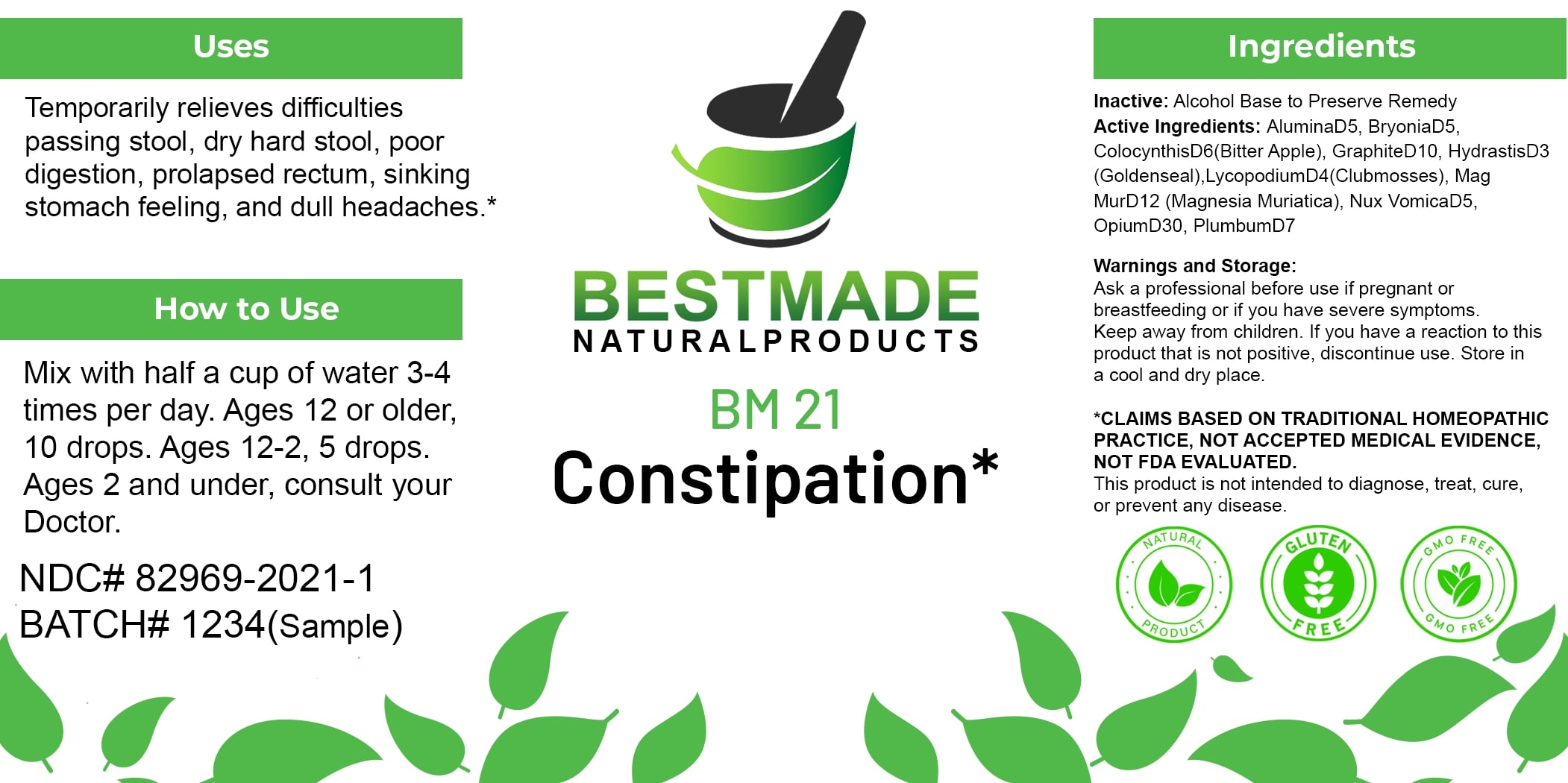 DRUG LABEL: Bestmade Natural Products BM21
NDC: 82969-2021 | Form: LIQUID
Manufacturer: Bestmade Natural Products
Category: homeopathic | Type: HUMAN OTC DRUG LABEL
Date: 20250122

ACTIVE INGREDIENTS: BRYONIA ALBA ROOT 30 [hp_C]/30 [hp_C]; GRAPHITE 30 [hp_C]/30 [hp_C]; LYCOPODIUM CLAVATUM SPORE 30 [hp_C]/30 [hp_C]; GOLDENSEAL 30 [hp_C]/30 [hp_C]; STRYCHNOS NUX-VOMICA SEED 30 [hp_C]/30 [hp_C]; CITRULLUS COLOCYNTHIS FRUIT PULP 30 [hp_C]/30 [hp_C]; ALUMINUM OXIDE 30 [hp_C]/30 [hp_C]; MAGNESIUM CHLORIDE 30 [hp_C]/30 [hp_C]; LEAD 30 [hp_C]/30 [hp_C]
INACTIVE INGREDIENTS: ALCOHOL 30 [hp_C]/30 [hp_C]

BM21

DOSAGE AND ADMINISTRATION

How to Use

Mix with half a cup of water 3-4 times per day. Ages 12 or older, 10 drops. Ages 12-2, 5 drops. Ages 2 and under, consult your Doctor.

Uses

Temporarily relieves difficulties passing stool, dry hard stool, poor digestion, prolapsed rectum, sinking stomach feeling, and dull headaches.*

*CLAIMS BASED ON TRADITIONAL HOMEOPATHIC PRACTICE, NOT ACCEPTED MEDICAL EVIDENCE, NOT FDA EVALUATED.
This product is not intended to diagnose, treat, cure, or prevent any disease.

INACTIVE INGREDIENT

Ingredients

Inactive: Alcohol Base to Preserve Remedy

Uses

Temporarily relieves difficulties passing stool, dry hard stool, poor digestion, prolapsed rectum, sinking stomach feeling, and dull headaches.*

*CLAIMS BASED ON TRADITIONAL HOMEOPATHIC PRACTICE, NOT ACCEPTED MEDICAL EVIDENCE, NOT FDA EVALUATED.
This product is not intended to diagnose, treat, cure, or prevent any disease.

KEEP OUT OF REACH OF CHILDREN

Warnings and Storage:

Ask a professional before use if pregnant or breastfeeding or if you have severe symptoms. Keep away from children. If you have a reaction to this product that is not positive, discontinue use. Store in a cool and dry place.

Active Ingredients:

Alumina D5, Bryonia D5, Colocynthis D6 (Bitter Apple), Graphite D10, Hydrastis D3 (Goldenseal), Lycopodium D4 (Clubmoss), Mag Mur D12 (Magnesia Muriatica), Nux Vomica D5, Opium D30, Plumbum D7

Warnings and Storage:

Ask a professional before use if pregnant or breastfeeding or if you have severe symptoms. Keep away from children. If you have a reaction to this product that is not positive, discontinue use. Store in a cool and dry place.

*CLAIMS BASED ON TRADITIONAL HOMEOPATHIC PRACTICE, NOT ACCEPTED MEDICAL EVIDENCE, NOT FDA EVALUATED.
This product is not intended to diagnose, treat, cure, or prevent any disease.

Entire package label